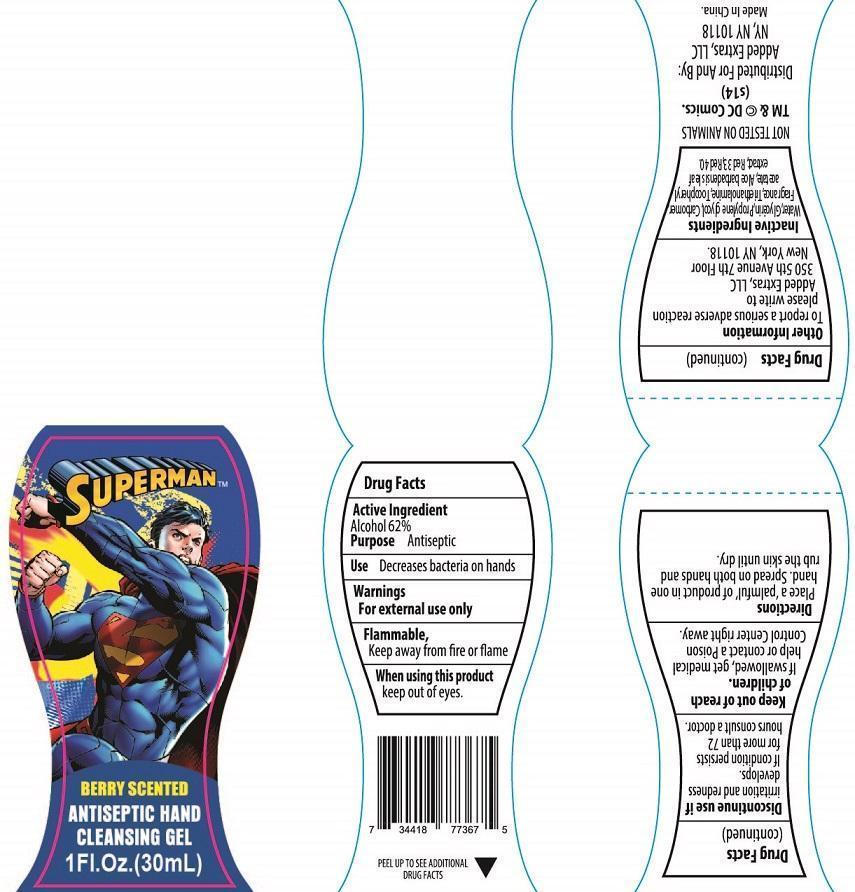 DRUG LABEL: Superman Berry Scented Antiseptic Hand Cleansing
NDC: 40104-262 | Form: GEL
Manufacturer: Ningbo Pulisi Daily Chemical Products Co., Ltd.
Category: otc | Type: HUMAN OTC DRUG LABEL
Date: 20140912

ACTIVE INGREDIENTS: ALCOHOL 62 mL/100 mL
INACTIVE INGREDIENTS: ALOE VERA LEAF; GLYCERIN; PROPYLENE GLYCOL; TOCOPHEROL; TROLAMINE; WATER

Drug Fact

Active Ingredient

Alcohol 62%

Purpose

Antiseptic

Uses

- decrease bacteria on hands

Warnings

For external use only

Use only as directed

Excessive use or prolonged exposure may cause irritation to skin.

Discontinue use if rash, redness or itching occurs.

Flammable. Keep away from fire or flame.

When using this product

- keep out of eyes.

Discontinue use if

irritation or redness develops. If condition persists for more than 72 hours, consult a doctor.

Keep out of reach of children.

If swallowed, get medical help or contact a Poison Control Center right away.

Directions

Place a Plmful of product in one hand, spread on both hands and rub the skin until dry.

Other Information

To report a serious adverse reaction, please write Added Extras, LLC, 350 tth Ave. 7th Floor, New York, NY 10118

Inactive Ingredients

aloe barbadensis gel, carbomer, fragrance, glycerin, propylene glycol, tocopherol, triethanolamine, water, Acetate, Fragrance, Red 33

Product Labeling

Made in China